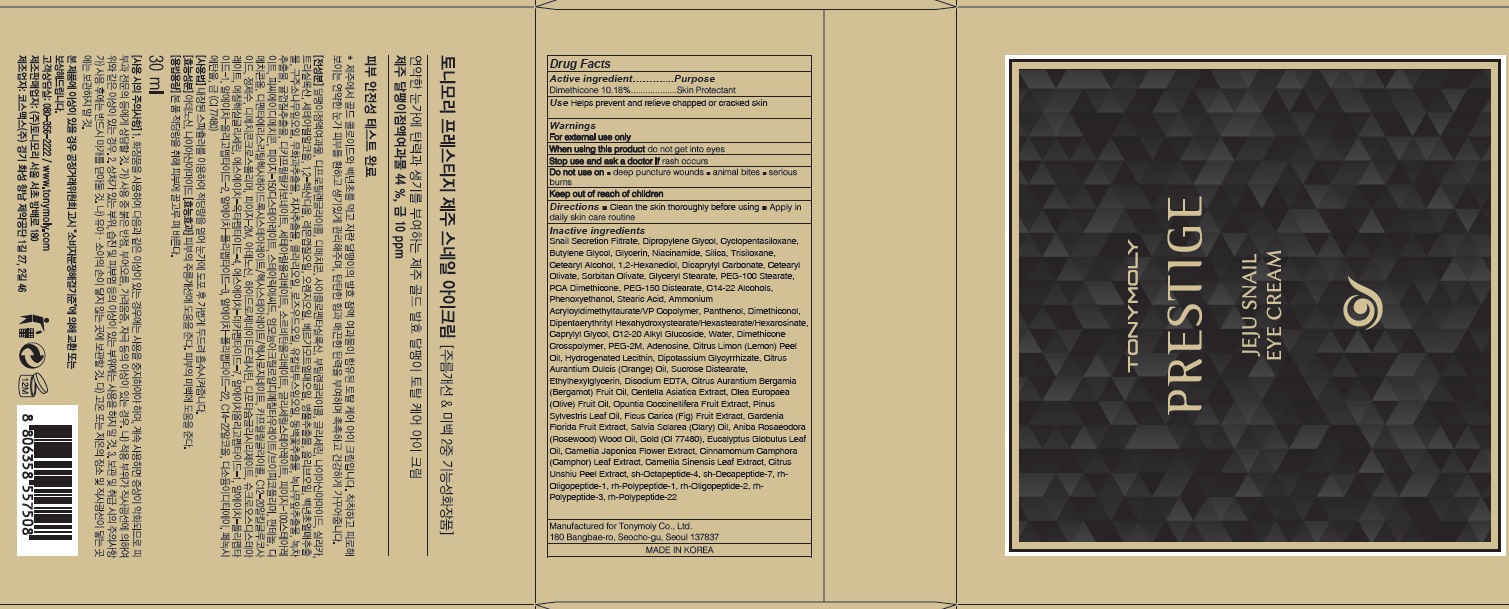 DRUG LABEL: PRESTIGE JEJU SNAIL EYE
NDC: 59078-317 | Form: CREAM
Manufacturer: TONYMOLY CO.,LTD
Category: otc | Type: HUMAN OTC DRUG LABEL
Date: 20160729

ACTIVE INGREDIENTS: Dimethicone 3.05 g/30 mL
INACTIVE INGREDIENTS: Dipropylene Glycol; Glycerin

ACTIVE INGREDIENT

Active Ingredient: Dimethicone 10.18%

INACTIVE INGREDIENT

Inactive Ingredients: Snail Secretion Filtrate, Dipropylene Glycol, Cyclopentasiloxane, Butylene Glycol, Glycerin, Niacinamide, Silica, Trisiloxane, Cetearyl Alcohol, 1,2-Hexanediol, Dicaprylyl Carbonate, Cetearyl Olivate, Sorbitan Olivate, Glyceryl Stearate, PEG-100 Stearate, PCA Dimethicone, PEG-150 Distearate, C14-22 Alcohols, Phenoxyethanol, Stearic Acid, Ammonium Acryloyldimethyltaurate/VP Copolymer, Panthenol, Dimethiconol, Dipentaerythrityl Hexahydroxystearate/Hexastearate/Hexarosinate, Caprylyl Glycol, C12-20 Alkyl Glucoside, Water, Dimethicone Crosspolymer, PEG-2M, Adenosine, Citrus Limon (Lemon) Peel Oil, Hydrogenated Lecithin, Dipotassium Glycyrrhizate, Citrus Aurantium Dulcis (Orange) Oil, Sucrose Distearate, Ethylhexylglycerin, Disodium EDTA, Citrus Aurantium Bergamia (Bergamot) Fruit Oil, Centella Asiatica Extract, Olea Europaea (Olive) Fruit Oil, Opuntia Coccinellifera Fruit Extract, Pinus Sylvestris Leaf Oil, Ficus Carica (Fig) Fruit Extract, Gardenia Florida Fruit Extract, Salvia Sclarea (Clary) Oil, Aniba Rosaeodora (Rosewood) Wood Oil, Gold (CI 77480), Eucalyptus Globulus Leaf Oil, Camellia Japonica Flower Extract, Cinnamomum Camphora (Camphor) Leaf Extract, Camellia Sinensis Leaf Extract, Citrus Unshiu Peel Extract, sh-Octapeptide-4, sh-Decapeptide-7, rh-Oligopeptide-1, rh-Polypeptide-1, rh-Oligopeptide-2, rh-Polypeptide-3, rh-Polypeptide-22

PURPOSE

Purpose: Skin Protectant

WARNINGS

Warnings: For external use only When using this product do not get into eyes, Stop use and ask a doctor if rash occurs Do not use on - deep puncture wounds - animal bites - serious burns Keep out of reach of children

KEEP OUT OF REACH OF CHILDREN

Use

Use: Helps prevent and relieve chapped or cracked skin

Directions

Directions: - Clean the skin thoroughly before using - Apply in daily skin care routine